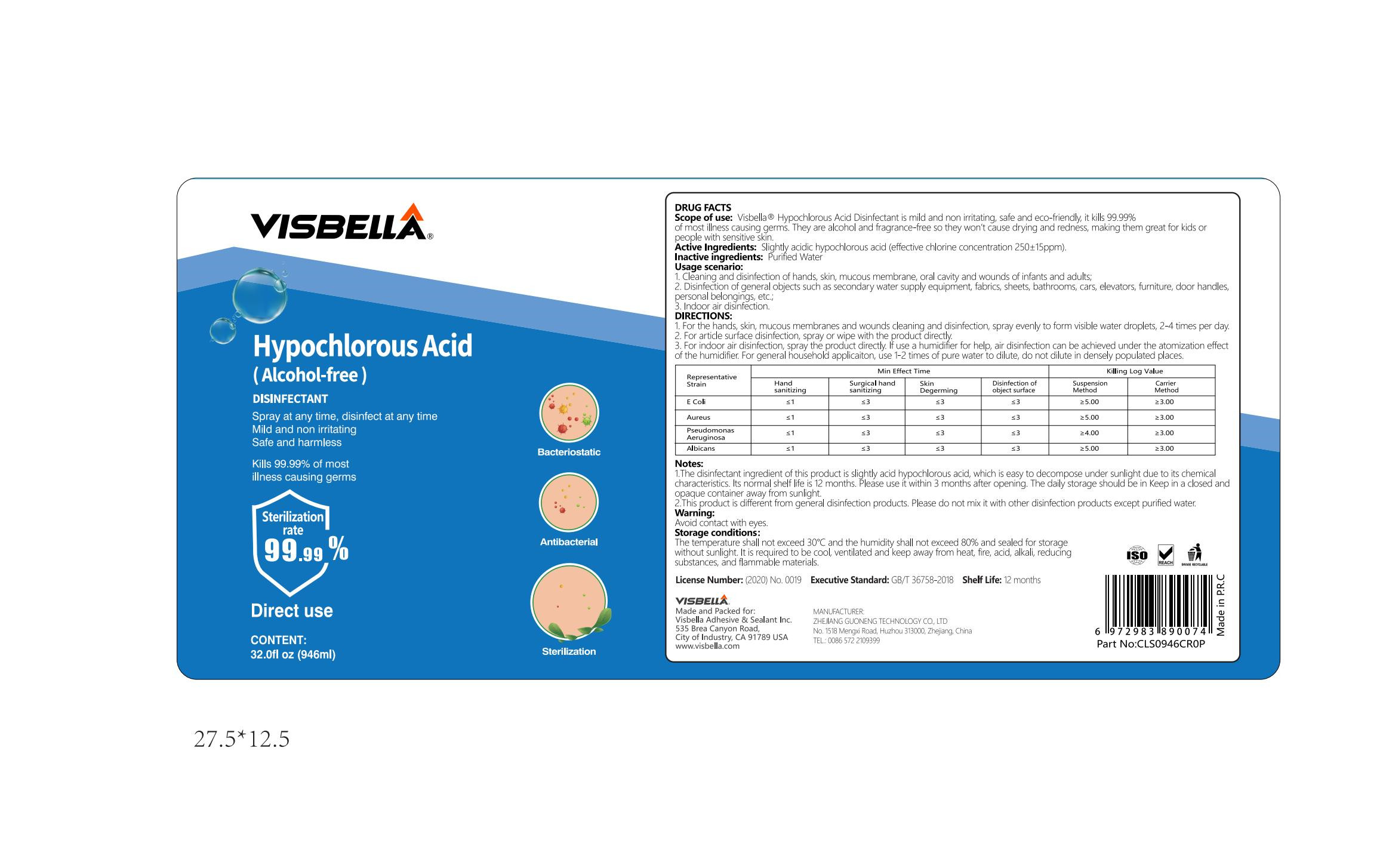 DRUG LABEL: Hypochlorous acid disinfecting
NDC: 40760-020 | Form: LIQUID
Manufacturer: Huzhou Guoneng New Material Co., Ltd.
Category: otc | Type: HUMAN OTC DRUG LABEL
Date: 20220214

ACTIVE INGREDIENTS: HYPOCHLOROUS ACID 236.5 mg/946 mL
INACTIVE INGREDIENTS: WATER

Usage scenario

1. Cleaning and disinfection of hands, skin , mucous membrane,oral cavity and wounds of infants and adults;
2. Disinfection of general objects such as secondary water supply equipment fabrics sheets, athrooms, cars,elevators, furniture, door handes,personal belongings,etc.;
3.Indoor air disinfection

PURPOSE

Spray at any time, disinfect at any time Mild and non irritating
Safe and harmless Kills 99.99% of mostillness causing germs

INACTIVE INGREDIENT

Purified Water

ACTIVE INGREDIENT

Slightly acidic hypochlorous acid (effective chlorine concentration 250±15ppm)

DIRECTIONS

1.For the hands,skin, mucous membranes and wounds cleaning and disinfection ,spray evenly to form vible water droplets,2-4 times per day

2.For article surface disinfection, spray or wipe with the product directly.
3.For indoor air disinfection, spray the product directly f use a humidfier for help, air disnfection can be achieved under the atomization effectof the humidfier For general household applicaiton, use 1-2 times of pure water to dilute, dio not dilute in densely populated places.

Storage conditions

The temperature shall not exceed 30°C and the humidity shall not exceed 80% and sealed for storage without sunlight. It is required to be cool, ventilated and keep away from heat,fire, acid, alkali, reducing substances, and flammable materials.

Keep out of reach of children

DO NOT USE

This product is different from general disinfection products.Please do not mikxit with other disinfection products except purified water

STOP USE

The disinfectant ingredient of this product is slichtly acid hypochlorous acid, which is easy to decompose under sunlight due to its chemicalcharactritics. t normal shelf lfe is 12 months Please use it within 3 months ater opening. The daily storage should be in Keep in a closed andopaque container away from sunlight.

WARNINGS

Avoid contact with eyes.